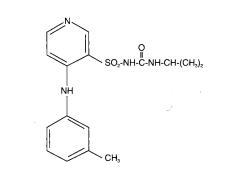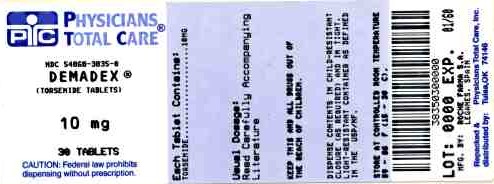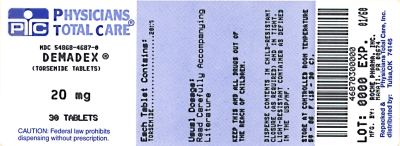 DRUG LABEL: Demadex
NDC: 54868-4687 | Form: TABLET
Manufacturer: Physicians Total Care, Inc.
Category: prescription | Type: HUMAN PRESCRIPTION DRUG LABEL
Date: 20090804

ACTIVE INGREDIENTS: TORSEMIDE 20 mg/1 1

DEMADEX® (torsemide) TABLETS

DESCRIPTION

DEMADEX® (torsemide) is a diuretic of the pyridine-sulfonylurea class. Its chemical name is 1-isopropyl-3-[(4-m-toluidino-3-pyridyl) sulfonyl]urea and its structural formula is:

Its empirical formula is C16H20N4O3S, its pKa is 7.1, and its molecular weight is 348.43.

Torsemide is a white to off-white crystalline powder. The tablets for oral administration also contain lactose NF, crospovidone NF, povidone USP, microcrystalline cellulose NF, and magnesium stearate NF.

CLINICAL PHARMACOLOGY

Mechanism of Action

Micropuncture studies in animals have shown that torsemide acts from within the lumen of the thick ascending portion of the loop of Henle, where it inhibits the Na^+/K^+/2CI^--carrier system. Clinical pharmacology studies have confirmed this site of action in humans, and effects in other segments of the nephron have not been demonstrated. Diuretic activity thus correlates better with the rate of drug excretion in the urine than with the concentration in the blood.

Torsemide increases the urinary excretion of sodium, chloride, and water, but it does not significantly alter glomerular filtration rate, renal plasma flow, or acid-base balance.

Pharmacokinetics and Metabolism

The bioavailability of DEMADEX tablets is approximately 80%, with little intersubject variation; the 90% confidence interval is 75% to 89%. The drug is absorbed with little first-pass metabolism, and the serum concentration reaches its peak (Cmax) within 1 hour after oral administration. Cmax and area under the serum concentration-time curve (AUC) after oral administration are proportional to dose over the range of 2.5 mg to 200 mg. Simultaneous food intake delays the time to Cmax by about 30 minutes, but overall bioavailability (AUC) and diuretic activity are unchanged. Absorption is essentially unaffected by renal or hepatic dysfunction.

The volume of distribution of torsemide is 12 liters to 15 liters in normal adults or in patients with mild to moderate renal failure or congestive heart failure. In patients with hepatic cirrhosis, the volume of distribution is approximately doubled.

In normal subjects the elimination half-life of torsemide is approximately 3.5 hours. Torsemide is cleared from the circulation by both hepatic metabolism (approximately 80% of total clearance) and excretion into the urine (approximately 20% of total clearance in patients with normal renal function). The major metabolite in humans is the carboxylic acid derivative, which is biologically inactive. Two of the lesser metabolites possess some diuretic activity, but for practical purposes metabolism terminates the action of the drug.

Because torsemide is extensively bound to plasma protein (greater than 99%), very little enters tubular urine via glomerular filtration. Most renal clearance of torsemide occurs via active secretion of the drug by the proximal tubules into tubular urine.

In patients with decompensated congestive heart failure, hepatic and renal clearance are both reduced, probably because of hepatic congestion and decreased renal plasma flow, respectively. The total clearance of torsemide is approximately 50% of that seen in healthy volunteers, and the plasma half-life and AUC are correspondingly increased. Because of reduced renal clearance, a smaller fraction of any given dose is delivered to the intraluminal site of action, so at any given dose there is less natriuresis in patients with congestive heart failure than in normal subjects.

In patients with renal failure, renal clearance of torsemide is markedly decreased but total plasma clearance is not significantly altered. A smaller fraction of the administered dose is delivered to the intraluminal site of action, and the natriuretic action of any given dose of diuretic is reduced. A diuretic response in renal failure may still be achieved if patients are given higher doses. The total plasma clearance and elimination half-life of torsemide remain normal under the conditions of impaired renal function because metabolic elimination by the liver remains intact.

In patients with hepatic cirrhosis, the volume of distribution, plasma half-life, and renal clearance are all increased, but total clearance is unchanged.

The pharmacokinetic profile of torsemide in healthy elderly subjects is similar to that in young subjects except for a decrease in renal clearance related to the decline in renal function that commonly occurs with aging. However, total plasma clearance and elimination half-life remain unchanged.

CLINICAL EFFECTS

With oral dosing, the onset of diuresis occurs within 1 hour and the peak effect occurs during the first or second hour and diuresis lasts about 6 to 8 hours. In healthy subjects given single doses, the dose-response relationship for sodium excretion is linear over the dose range of 2.5 mg to 20 mg. The increase in potassium excretion is negligible after a single dose of up to 10 mg and only slight (5 mEq to 15 mEq) after a single dose of 20 mg.

Congestive Heart Failure
DEMADEX has been studied in controlled trials in patients with New York Heart Association Class II to Class IV congestive heart failure. Patients who received 10 mg to 20 mg of daily DEMADEX in these studies achieved significantly greater reductions in weight and edema than did patients who received placebo.

Nonanuric Renal Failure
In single-dose studies in patients with nonanuric renal failure, high doses of DEMADEX (20 mg to 200 mg) caused marked increases in water and sodium excretion. In patients with nonanuric renal failure, severe enough to require hemodialysis, chronic treatment with up to 200 mg of daily DEMADEX has not been shown to change steady-state fluid retention. When patients in a study of acute renal failure received total daily doses of 520 mg to 1200 mg of DEMADEX, 19% experienced seizures. Ninety-six patients were treated in this study; 6/32 treated with torsemide experienced seizures, 6/32 treated with comparably high doses of furosemide experienced seizures, and 1/32 treated with placebo experienced a seizure.

Hepatic Cirrhosis
When given with aldosterone antagonists, DEMADEX also caused increases in sodium and fluid excretion in patients with edema or ascites due to hepatic cirrhosis. Urinary sodium excretion rate relative to the urinary excretion rate of DEMADEX is less in cirrhotic patients than in healthy subjects (possibly because of the hyperaldosteronism and resultant sodium retention that are characteristic of portal hypertension and ascites). However, because of the increased renal clearance of DEMADEX in patients with hepatic cirrhosis, these factors tend to balance each other, and the result is an overall natriuretic response that is similar to that seen in healthy subjects. Chronic use of any diuretic in hepatic disease has not been studied in adequate and well-controlled trials.

Essential Hypertension
In patients with essential hypertension, DEMADEX has been shown in controlled studies to lower blood pressure when administered once a day at doses of 5 mg to 10 mg. The antihypertensive effect is near maximal after 4 to 6 weeks of treatment, but it may continue to increase for up to 12 weeks. Systolic and diastolic supine and standing blood pressures are all reduced. There is no significant orthostatic effect, and there is only a minimal peak-trough difference in blood pressure reduction.

The antihypertensive effects of DEMADEX are, like those of other diuretics, on the average greater in black patients (a low-renin population) than in nonblack patients.

When DEMADEX is first administered, daily urinary sodium excretion increases for at least a week. With chronic administration, however, daily sodium loss comes into balance with dietary sodium intake. If the administration of DEMADEX is suddenly stopped, blood pressure returns to pretreatment levels over several days, without overshoot.

DEMADEX has been administered together with β-adrenergic blocking agents, ACE inhibitors, and calcium-channel blockers. Adverse drug interactions have not been observed, and special dosage adjustment has not been necessary.

INDICATIONS AND USAGE

DEMADEX is indicated for the treatment of edema associated with congestive heart failure, renal disease, or hepatic disease. Use of torsemide has been found to be effective for the treatment of edema associated with chronic renal failure. Chronic use of any diuretic in hepatic disease has not been studied in adequate and well-controlled trials.

DEMADEX is indicated for the treatment of hypertension alone or in combination with other antihypertensive agents.

CONTRAINDICATIONS

DEMADEX is contraindicated in patients with known hypersensitivity to DEMADEX or to sulfonylureas.

DEMADEX is contraindicated in patients who are anuric.

WARNINGS

Hepatic Disease With Cirrhosis and Ascites
DEMADEX should be used with caution in patients with hepatic disease with cirrhosis and ascites, since sudden alterations of fluid and electrolyte balance may precipitate hepatic coma. In these patients, diuresis with DEMADEX (or any other diuretic) is best initiated in the hospital. To prevent hypokalemia and metabolic alkalosis, an aldosterone antagonist or potassium-sparing drug should be used concomitantly with DEMADEX.

Ototoxicity
Tinnitus and hearing loss (usually reversible) have been observed after rapid intravenous injection of other loop diuretics and have also been observed after oral DEMADEX. It is not certain that these events were attributable to DEMADEX. Ototoxicity has also been seen in animal studies when very high plasma levels of torsemide were induced.

Volume and Electrolyte Depletion
Patients receiving diuretics should be observed for clinical evidence of electrolyte imbalance, hypovolemia, or prerenal azotemia. Symptoms of these disturbances may include one or more of the following: dryness of the mouth, thirst, weakness, lethargy, drowsiness, restlessness, muscle pains or cramps, muscular fatigue, hypotension, oliguria, tachycardia, nausea, and vomiting. Excessive diuresis may cause dehydration, blood-volume reduction, and possibly thrombosis and embolism, especially in elderly patients. In patients who develop fluid and electrolyte imbalances, hypovolemia, or prerenal azotemia, the observed laboratory changes may include hyper- or hyponatremia, hyper- or hypochloremia, hyper- or hypokalemia, acid-base abnormalities, and increased blood urea nitrogen (BUN). If any of these occur, DEMADEX should be discontinued until the situation is corrected; DEMADEX may be restarted at a lower dose.

In controlled studies in the United States, DEMADEX was administered to hypertensive patients at doses of 5 mg or 10 mg daily. After 6 weeks at these doses, the mean decrease in serum potassium was approximately 0.1 mEq/L. The percentage of patients who had a serum potassium level below 3.5 mEq/L at any time during the studies was essentially the same in patients who received DEMADEX (1.5%) as in those who received placebo (3%). In patients followed for 1 year, there was no further change in mean serum potassium levels. In patients with congestive heart failure, hepatic cirrhosis, or renal disease treated with DEMADEX at doses higher than those studied in United States antihypertensive trials, hypokalemia was observed with greater frequency, in a dose-related manner.

In patients with cardiovascular disease, especially those receiving digitalis glycosides, diuretic-induced hypokalemia may be a risk factor for the development of arrhythmias. The risk of hypokalemia is greatest in patients with cirrhosis of the liver, in patients experiencing a brisk diuresis, in patients who are receiving inadequate oral intake of electrolytes, and in patients receiving concomitant therapy with corticosteroids or ACTH.

Periodic monitoring of serum potassium and other electrolytes is advised in patients treated with DEMADEX.

PRECAUTIONS

Laboratory Values

Potassium: See WARNINGS

Calcium
Single doses of DEMADEX increased the urinary excretion of calcium by normal subjects, but serum calcium levels were slightly increased in 4- to 6-week hypertension trials. In a long-term study of patients with congestive heart failure, the average 1-year change in serum calcium was a decrease of 0.10 mg/dL (0.02 mmol/L). Among 426 patients treated with DEMADEX for an average of 11 months, hypocalcemia was not reported as an adverse event.

Magnesium
Single doses of DEMADEX caused healthy volunteers to increase their urinary excretion of magnesium, but serum magnesium levels were slightly increased in 4- to 6-week hypertension trials. In long-term hypertension studies, the average 1-year change in serum magnesium was an increase of 0.03 mg/dL (0.01 mmol/L). Among 426 patients treated with DEMADEX for an average of 11 months, one case of hypomagnesemia (1.3 mg/dL [0.53 mmol/L]) was reported as an adverse event.

In a long-term clinical study of DEMADEX in patients with congestive heart failure, the estimated annual change in serum magnesium was an increase of 0.2 mg/dL (0.08 mmol/L), but these data are confounded by the fact that many of these patients received magnesium supplements. In a 4-week study in which magnesium supplementation was not given, the rate of occurrence of serum magnesium levels below 1.7 mg/dL (0.70 mmol/L) was 6% and 9% in the groups receiving 5 mg and 10 mg of DEMADEX, respectively.

Blood Urea Nitrogen (BUN), Creatinine and Uric Acid
DEMADEX produces small dose-related increases in each of these laboratory values. In hypertensive patients who received 10 mg of DEMADEX daily for 6 weeks, the mean increase in blood urea nitrogen was 1.8 mg/dL (0.6 mmol/L), the mean increase in serum creatinine was 0.05 mg/dL (4 mmol/L), and the mean increase in serum uric acid was 1.2 mg/dL (70 mmol/L). Little further change occurred with long-term treatment, and all changes reversed when treatment was discontinued.

Symptomatic gout has been reported in patients receiving DEMADEX, but its incidence has been similar to that seen in patients receiving placebo.

Glucose
Hypertensive patients who received 10 mg of daily DEMADEX experienced a mean increase in serum glucose concentration of 5.5 mg/dL (0.3 mmol/L) after 6 weeks of therapy, with a further increase of 1.8 mg/dL (0.1 mmol/L) during the subsequent year. In long-term studies in diabetics, mean fasting glucose values were not significantly changed from baseline. Cases of hyperglycemia have been reported but are uncommon.

Serum Lipids
In the controlled short-term hypertension studies in the United States, daily doses of 5 mg, 10 mg, and 20 mg of DEMADEX were associated with increases in total plasma cholesterol of 4, 4, and 8 mg/dL (0.10 to 0.20 mmol/L), respectively. The changes subsided during chronic therapy.

In the same short-term hypertension studies, daily doses of 5 mg, 10 mg and 20 mg of DEMADEX were associated with mean increases in plasma triglycerides of 16, 13 and 71 mg/dL (0.15 to 0.80 mmol/L), respectively.

In long-term studies of 5 mg to 20 mg of DEMADEX daily, no clinically significant differences from baseline lipid values were observed after 1 year of therapy.

Other
In long-term studies in hypertensive patients, DEMADEX has been associated with small mean decreases in hemoglobin, hematocrit, and erythrocyte count and small mean increases in white blood cell count, platelet count, and serum alkaline phosphatase. Although statistically significant, all of these changes were medically inconsequential. No significant trends have been observed in any liver enzyme tests other than alkaline phosphatase.

Drug Interactions

In patients with essential hypertension, DEMADEX has been administered together with beta-blockers, ACE inhibitors, and calcium-channel blockers. In patients with congestive heart failure, DEMADEX has been administered together with digitalis glycosides, ACE inhibitors, and organic nitrates. None of these combined uses was associated with new or unexpected adverse events.

Torsemide does not affect the protein binding of glyburide or of warfarin, the anticoagulant effect of phenprocoumon (a related coumarin derivative), or the pharmacokinetics of digoxin or carvedilol (a vasodilator/beta-blocker). In healthy subjects, coadministration of DEMADEX was associated with significant reduction in the renal clearance of spironolactone, with corresponding increases in the AUC. However, clinical experience indicates that dosage adjustment of either agent is not required.

Because DEMADEX and salicylates compete for secretion by renal tubules, patients receiving high doses of salicylates may experience salicylate toxicity when DEMADEX is concomitantly administered. Also, although possible interactions between torsemide and nonsteroidal anti-inflammatory agents (including aspirin) have not been studied, coadministration of these agents with another loop diuretic (furosemide) has occasionally been associated with renal dysfunction.

The natriuretic effect of DEMADEX (like that of many other diuretics) is partially inhibited by the concomitant administration of indomethacin. This effect has been demonstrated for DEMADEX under conditions of dietary sodium restriction (50 mEq/day) but not in the presence of normal sodium intake (150 mEq/day).

The pharmacokinetic profile and diuretic activity of torsemide are not altered by cimetidine or spironolactone. Coadministration of digoxin is reported to increase the area under the curve for torsemide by 50%, but dose adjustment of DEMADEX is not necessary.

Concomitant use of torsemide and cholestyramine has not been studied in humans but, in a study in animals, coadministration of cholestyramine decreased the absorption of orally administered torsemide. If DEMADEX and cholestyramine are used concomitantly, simultaneous administration is not recommended.

Coadministration of probenecid reduces secretion of DEMADEX into the proximal tubule and thereby decreases the diuretic activity of DEMADEX.

Other diuretics are known to reduce the renal clearance of lithium, inducing a high risk of lithium toxicity, so coadministration of lithium and diuretics should be undertaken with great caution, if at all. Coadministration of lithium and DEMADEX has not been studied.

Other diuretics have been reported to increase the ototoxic potential of aminoglycoside antibiotics and of ethacrynic acid, especially in the presence of impaired renal function. These potential interactions with DEMADEX have not been studied.

Carcinogenesis, Mutagenesis, Impairment of Fertility

No overall increase in tumor incidence was found when torsemide was given to rats and mice throughout their lives at doses up to 9 mg/kg/day (rats) and 32 mg/kg/day (mice). On a body-weight basis, these doses are 27 to 96 times a human dose of 20 mg; on a body-surface-area basis, they are 5 to 8 times this dose. In the rat study, the high-dose female group demonstrated renal tubular injury, interstitial inflammation, and a statistically significant increase in renal adenomas and carcinomas. The tumor incidence in this group was, however, not much higher than the incidence sometimes seen in historical controls. Similar signs of chronic non-neoplastic renal injury have been reported in high-dose animal studies of other diuretics such as furosemide and hydrochlorothiazide.

No mutagenic activity was detected in any of a variety of in vivo and in vitro tests of torsemide and its major human metabolite. The tests included the Ames test in bacteria (with and without metabolic activation), tests for chromosome aberrations and sister-chromatid exchanges in human lymphocytes, tests for various nuclear anomalies in cells found in hamster and murine bone marrow, tests for unscheduled DNA synthesis in mice and rats, and others.

In doses up to 25 mg/kg/day (75 times a human dose of 20 mg on a body-weight basis; 13 times this dose on a body-surface-area basis), torsemide had no adverse effect on the reproductive performance of male or female rats.

Pregnancy

Pregnancy Category B

There was no fetotoxicity or teratogenicity in rats treated with up to 5 mg/kg/day of torsemide (on a mg/kg basis, this is 15 times a human dose of 20 mg/day; on a mg/m2 basis, the animal dose is 10 times the human dose), or in rabbits, treated with 1.6 mg/kg/day (on a mg/kg basis, 5 times the human dose of 20 mg/kg/day; on a mg/m2 basis, 1.7 times this dose). Fetal and maternal toxicity (decrease in average body weight, increase in fetal resorption and delayed fetal ossification) occurred in rabbits and rats given doses 4 (rabbits) and 5 (rats) times larger. Adequate and well-controlled studies have not been carried out in pregnant women. Because animal reproduction studies are not always predictive of human response, this drug should be used during pregnancy only if clearly needed.

Labor and Delivery

The effect of DEMADEX on labor and delivery is unknown.

Nursing Mothers

It is not known whether DEMADEX is excreted in human milk. Because many drugs are excreted in human milk, caution should be exercised when DEMADEX is administered to a nursing woman.

Pediatric Use

Safety and effectiveness in pediatric patients have not been established.

Administration of another loop diuretic to severely premature infants with edema due to patent ductus arteriosus and hyaline membrane disease has occasionally been associated with renal calcifications, sometimes barely visible on X-ray but sometimes in staghorn form, filling the renal pelves. Some of these calculi have been dissolved, and hypercalciuria has been reported to have decreased, when chlorothiazide has been coadministered along with the loop diuretic. In other premature neonates with hyaline membrane disease, another loop diuretic has been reported to increase the risk of persistent patent ductus arteriosus, possibly through a prostaglandin-E-mediated process. The use of DEMADEX in such patients has not been studied.

Geriatric use

Of the total number of patients who received DEMADEX in United States clinical studies, 24% were 65 or older while about 4% were 75 or older. No specific age-related differences in effectiveness or safety were observed between younger patients and elderly patients.

ADVERSE REACTIONS

To report SUSPECTED ADVERSE REACTIONS, contact Meda Pharmaceuticals Inc. at 1-800-526-3840 or FDA at 1-800-FDA-1088 or www.fda.gov/medwatch.

At the time of approval, DEMADEX had been evaluated for safety in approximately 4000 subjects: over 800 of these subjects received DEMADEX for at least 6 months, and over 380 were treated for more than 1 year. Among these subjects were 564 who received DEMADEX during United States-based trials in which 274 other subjects received placebo.

The reported side effects of DEMADEX were generally transient, and there was no relationship between side effects and age, sex, race, or duration of therapy. Discontinuation of therapy due to side effects occurred in 3.5% of United States patients treated with DEMADEX and in 4.4% of patients treated with placebo. In studies conducted in the United States and Europe, discontinuation rates due to side effects were 3.0% (38/1250) with DEMADEX and 3.4% (13/380) with furosemide in patients with congestive heart failure, 2.0% (8/409) with DEMADEX and 4.8% (11/230) with furosemide in patients with renal insufficiency, and 7.6% (13/170) with DEMADEX and 0% (0/33) with furosemide in patients with cirrhosis.

The most common reasons for discontinuation of therapy with DEMADEX were (in descending order of frequency) dizziness, headache, nausea, weakness, vomiting, hyperglycemia, excessive urination, hyperuricemia, hypokalemia, excessive thirst, hypovolemia, impotence, esophageal hemorrhage, and dyspepsia. Dropout rates for these adverse events ranged from 0.1% to 0.5%.

The side effects considered possibly or probably related to study drug that occurred in United States placebo-controlled trials in more than 1% of patients treated with DEMADEX are shown in Table 1.

Table 1 Reactions Possibly or Probably Drug-Related United States Placebo-Controlled Studies Incidence (Percentages of Patients)
 | DEMADEX (N=564) | Placebo (N=274)
Headache | 7.3 | 9.1
Excessive Urination | 6.7 | 2.2
Dizziness | 3.2 | 4.0
Rhinitis | 2.8 | 2.2
Asthenia | 2.0 | 1.5
Diarrhea | 2.0 | 1.1
ECG Abnormality | 2.0 | 0.4
Cough Increase | 2.0 | 1.5
Constipation | 1.8 | 0.7
Nausea | 1.8 | 0.4
Arthralgia | 1.8 | 0.7
Dyspepsia | 1.6 | 0.7
Sore Throat | 1.6 | 0.7
Myalgia | 1.6 | 1.5
Chest Pain | 1.2 | 0.4
Insomnia | 1.2 | 1.8
Edema | 1.1 | 1.1
Nervousness | 1.1 | 0.4

The daily doses of DEMADEX used in these trials ranged from 1.25 mg to 20 mg, with most patients receiving 5 mg to 10 mg; the duration of treatment ranged from 1 to 52 days, with a median of 41 days. Of the side effects listed in the table, only “excessive urination” occurred significantly more frequently in patients treated with DEMADEX than in patients treated with placebo. In the placebo-controlled hypertension studies whose design allowed side-effect rates to be attributed to dose, excessive urination was reported by 1% of patients receiving placebo, 4% of those treated with 5 mg of daily DEMADEX, and 15% of those treated with 10 mg. The complaint of excessive urination was generally not reported as an adverse event among patients who received DEMADEX for cardiac, renal, or hepatic failure.

Serious adverse events reported in the clinical studies for which a drug relationship could not be excluded were atrial fibrillation, chest pain, diarrhea, digitalis intoxication, gastrointestinal hemorrhage, hyperglycemia, hyperuricemia, hypokalemia, hypotension, hypovolemia, shunt thrombosis, rash, rectal bleeding, syncope, and ventricular tachycardia.

Angioedema has been reported in a patient exposed to DEMADEX who was later found to be allergic to sulfa drugs.

Of the adverse reactions during placebo-controlled trials listed without taking into account assessment of relatedness to drug therapy, arthritis and various other nonspecific musculoskeletal problems were more frequently reported in association with DEMADEX than with placebo, even though gout was somewhat more frequently associated with placebo. These reactions did not increase in frequency or severity with the dose of DEMADEX. One patient in the group treated with DEMADEX withdrew due to myalgia, and one in the placebo group withdrew due to gout.

Hypokalemia: See WARNINGS

OVERDOSAGE

There is no human experience with overdoses of DEMADEX, but the signs and symptoms of overdosage can be anticipated to be those of excessive pharmacologic effect: dehydration, hypovolemia, hypotension, hyponatremia, hypokalemia, hypochloremic alkalosis, and hemoconcentration. Treatment of overdosage should consist of fluid and electrolyte replacement.

Laboratory determinations of serum levels of torsemide and its metabolites are not widely available.

No data are available to suggest physiological maneuvers (e.g., maneuvers to change the pH of the urine) that might accelerate elimination of torsemide and its metabolites. Torsemide is not dialyzable, so hemodialysis will not accelerate elimination.

DOSAGE AND ADMINISTRATION

General

DEMADEX tablets may be given at any time in relation to a meal, as convenient. Special dosage adjustment in the elderly is not necessary.

Congestive Heart Failure

The usual initial dose of DEMADEX is 10 mg or 20 mg of once-daily oral DEMADEX. If the diuretic response is inadequate, the dose should be titrated upward by approximately doubling until the desired diuretic response is obtained. Single doses higher than 200 mg have not been adequately studied.

Chronic Renal Failure

The usual initial dose of DEMADEX is 20 mg of once-daily oral DEMADEX. If the diuretic response is inadequate, the dose should be titrated upward by approximately doubling until the desired diuretic response is obtained. Single doses higher than 200 mg have not been adequately studied.

Hepatic Cirrhosis

The usual initial dose is 5 mg or 10 mg of once-daily oral DEMADEX, administered together with an aldosterone antagonist or a potassium-sparing diuretic. If the diuretic response is inadequate, the dose should be titrated upward by approximately doubling until the desired diuretic response is obtained. Single doses higher than 40 mg have not been adequately studied.

Chronic use of any diuretic in hepatic disease has not been studied in adequate and well-controlled trials.

Hypertension

The usual initial dose is 5 mg once daily. If the 5 mg dose does not provide adequate reduction in blood pressure within 4 to 6 weeks, the dose may be increased to 10 mg once daily. If the response to 10 mg is insufficient, an additional antihypertensive agent should be added to the treatment regimen.

HOW SUPPLIED

DEMADEX for oral administration is available as white, scored tablets containing 10 mg, 20 mg of torsemide.

The tablets are supplied in:

10 mg Bottles of 30 NDC 54868-3835-0

20 mg Bottles of 10 NDC 54868-4687-1
20 mg Bottles of 30 NDC 54868-4687-0
20 mg Bottles of 90 NDC 54868-4687-3
20 mg Bottles of 100 NDC 54868-4687-2

Each tablet is debossed on the scored side with the logo BM and 102, 103, 104, or 105 (for 5 mg, 10 mg, 20 mg, or 100 mg, respectively). On the opposite side, the tablet is debossed with 5, 10, 20, or 100 to indicate the dose.

Storage
Store at 15° to 30°C (59° to 86°F).

Rx only

PACKAGE LABEL

Demadex Tablets, 10 mg
Demadex Tablets, 20 mg